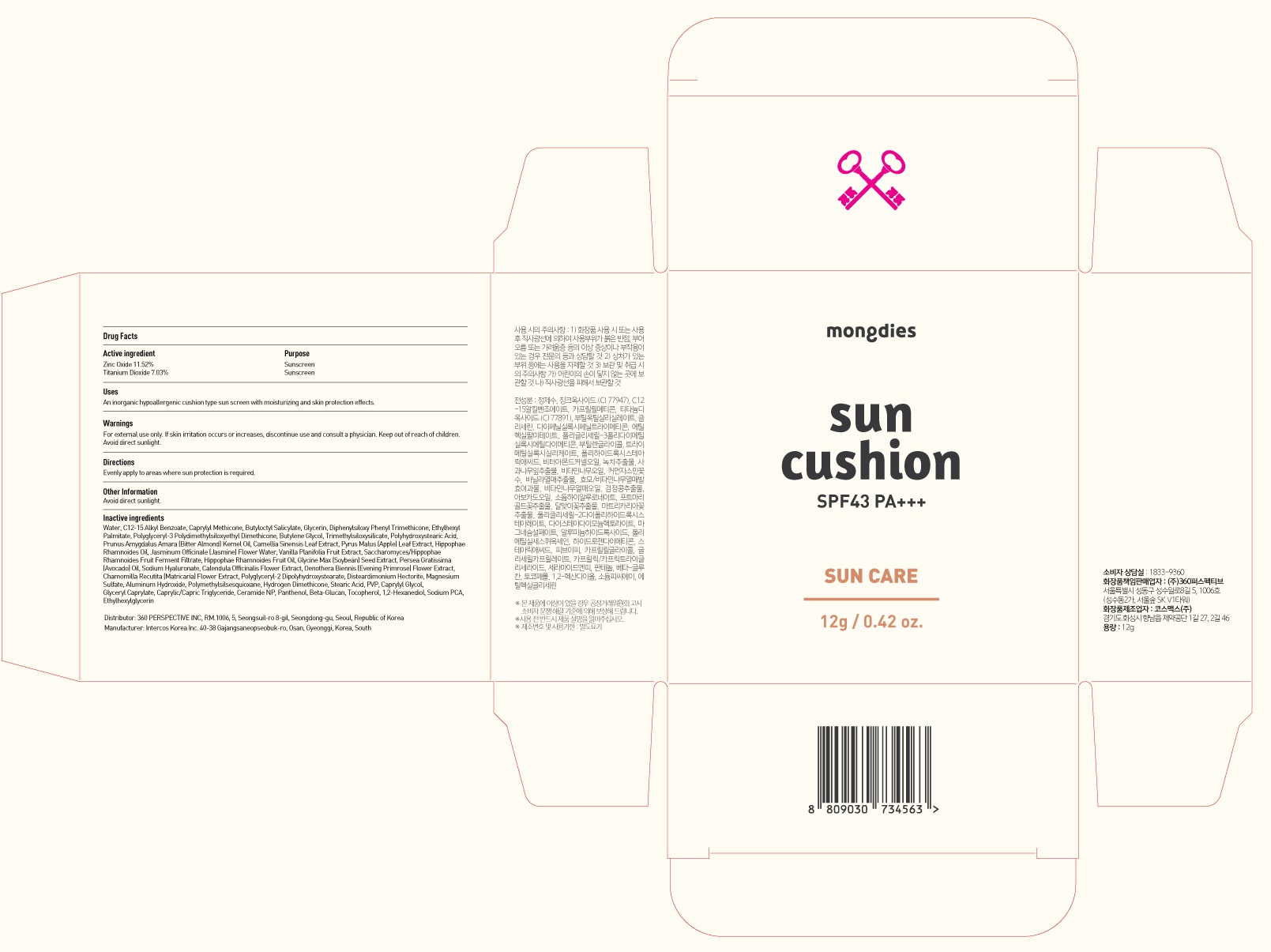 DRUG LABEL: Mongdies excellent sun cushion
NDC: 70477-040 | Form: POWDER
Manufacturer: 360Perspective Inc.
Category: otc | Type: HUMAN OTC DRUG LABEL
Date: 20210910

ACTIVE INGREDIENTS: Zinc Oxide 1.38 g/12 g; Titanium Dioxide 0.84 g/12 g
INACTIVE INGREDIENTS: Water; ALKYL (C12-15) BENZOATE; CAPRYLYL TRISILOXANE

ACTIVE INGREDIENT

Zinc Oxide 11.52%
Titanium Dioxide 7.03%

PURPOSE

Sunscreen

WARNINGS

For external use only. If skin irritation occurs or increases, discontinue use and consult a physician. Keep out of reach of children. Avoid direct sunlight.

KEEP OUT OF REACH OF CHILDREN

Uses

An inorganic hypoallergenic cushion type sun screen with moisturizing and skin protection effects.

Directions

Evenly apply to areas when sun protection is required.

Other Information

Avoid direct sunlight.

INACTIVE INGREDIENTS

Water, C12-15 Alkyl Benzoate, Caprylyl Methicone, Butyloctyl Salicylate, Glycerin, Diphenylsiloxy Phenyl Trimethicone, Ethylhexyl Palmitate, Polyglyceryl-3 Polydimethylsiloxyethyl Dimethicone, Butylene Glycol, Trimethylsiloxysilicate, Polyhydroxystearic Acid, Prunus Amygdalus Amara (Bitter Almond) Kernel Oil, Camellia Sinensis Leaf Extract, Pyrus Malus (Apple) Leaf Extract, Hippophae Rhamnoides Oil, Jasminum Officinale (Jasmine) Flower Water, Vanilla Planifolia Fruit Extract, Saccharomyces/Hippophae Rhamnoides Fruit Ferment Filtrate, Hippophae Rhamnoides Fruit Oil, Glycine Max (Soybean) Seed Extract, Persea Gratissima (Avocado) Oil, Sodium Hyaluronate, Calendula Officinalis Flower Extract, Oenothera Biennis (Evening Primrose) Flower Extract, Chamomilla Recutita (Matricaria) Flower Extract, Polyglyceryl-2 Dipolyhydroxystearate, Disteardimonium Hectorite, Magnesium Sulfate, Aluminum Hydroxide, Polymethylsilsesquioxane, Hydrogen Dimethicone, Stearic Acid, PVP, Caprylyl Glycol, Glyceryl Caprylate, Caprylic/Capric Triglyceride, Ceramide NP, Panthenol, Beta-Glucan, Tocopherol, 1,2-Hexanediol, Sodium PCA, Ethylhexylglycerin